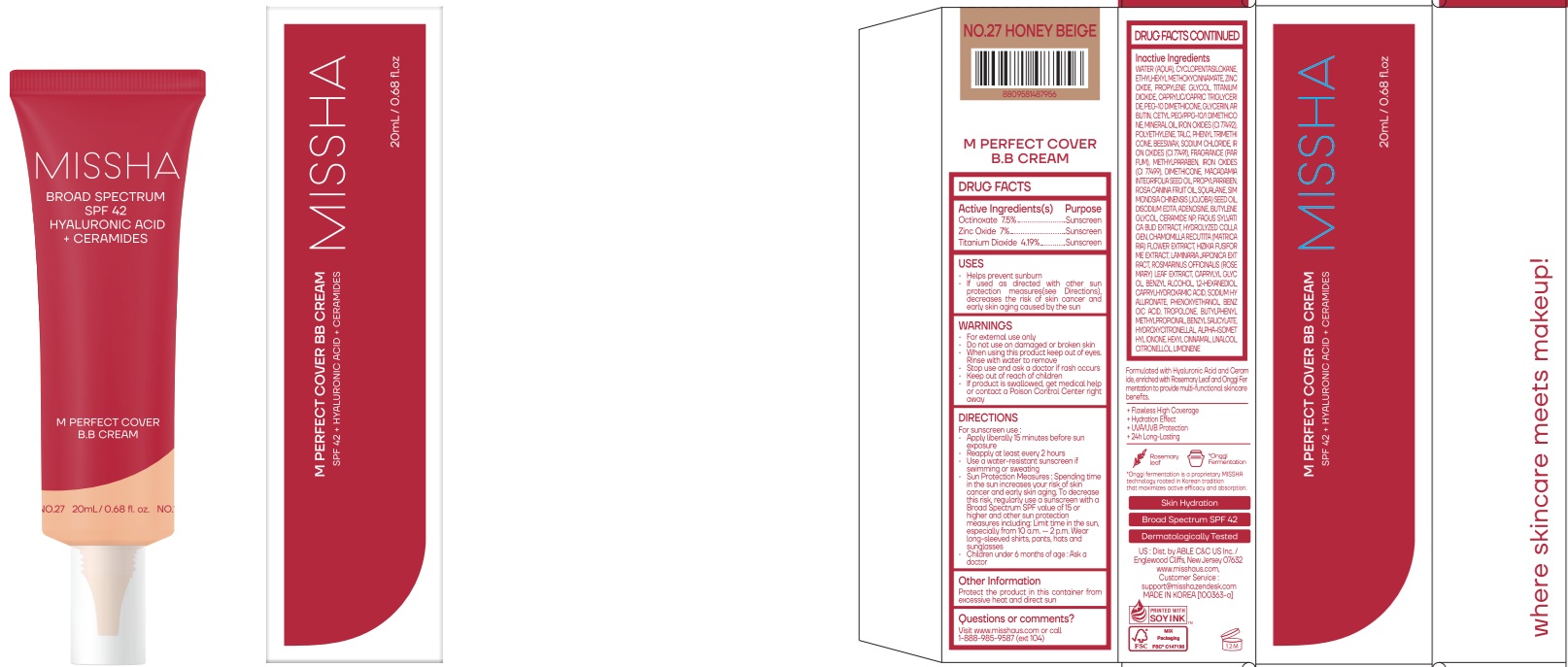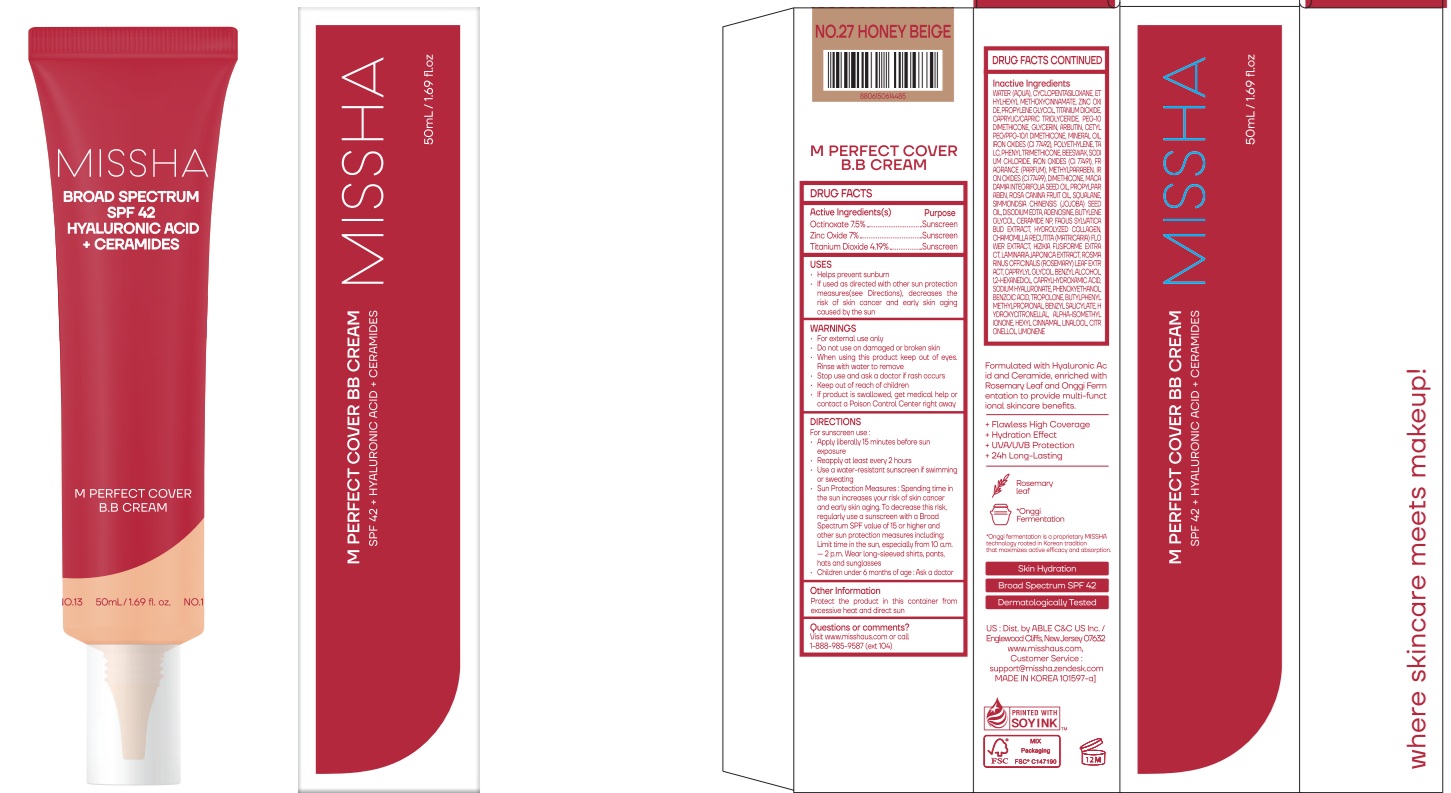 DRUG LABEL: MISSHA M Perfect Cover BB No.27
NDC: 13733-254 | Form: CREAM
Manufacturer: Able C&C Co., Ltd.
Category: otc | Type: HUMAN OTC DRUG LABEL
Date: 20260206

ACTIVE INGREDIENTS: ZINC OXIDE 7 g/100 mL; OCTINOXATE 7.5 g/100 mL; TITANIUM DIOXIDE 4.19 g/100 mL
INACTIVE INGREDIENTS: WATER; CAPRYLIC/CAPRIC TRIGLYCERIDE; CYCLOMETHICONE 5

MISSHA M Perfect Cover BB Cream NO.27 20mL, 50mL

Active ingredient(s)

Octinoxate 7.5%

Zinc Oxide 7%

Titanium Dioxide 4.19%

Purpose

Sunscreen

USES

· Helps prevent sunburn

· If used as directed with other sun protection measures (see Directions), decreases the risk of skin cancer and early skin aging caused by the sun

WARNINGS

· For external use only.

· Do not use on damaged or broken skin.

· When using this product keep out of eyes. Rinse with water to remove.

· Stop use and ask a doctor if rash occurs

· Keep out of reach of children.

· If product is swallowed, get medical help or contact a Poison Control Center right away.

Keep out of reach of children.

DIRECTIONS

For sunscreen use:

· Apply liberally 15 minutes before sun exposure

· Reapply at least every 2 hours

· Use a water-resistant sunscreen if swimming or sweating

· Sun Protection Measures. Spending time in the sun increases your risk of skin cancer and early skin aging. To decrease this risk, regularly use a sunscreen with SPF value of 15 or higher and other sun protection measures including:

* Limit time in the sun, especially from 10a.m.-2p.m.

* Wear long-sleeved shirts, pants, hats and sunglasses

· Children under 6 months of age: Ask a doctor

Other Information

Protect the product in this container from excessive heat and direct sun

Questions or comments?

Visit www.misshaus.com or call 1-888-985-9587 (ext 104)

Inactive ingredients

WATER (AQUA), CYCLOPENTASILOXANE, PROPYLENE GLYCOL, CAPRYLIC/CAPRIC TRIGLYCERIDE, PEG-10 DIMETHICONE, GLYCERIN, ARBUTIN, CETYL PEG/PPG-10/1 DIMETHICONE, MINERAL OIL, IRON OXIDES (CI 77492), POLYETHYLENE, TALC, PHENYL TRIMETHICONE, BEESWAX, SODIUM CHLORIDE, IRON OXIDES (CI 77491), FRAGRANCE (PARFUM), METHYLPARABEN, IRON OXIDES (CI 77499), DIMETHICONE, MACADAMIA INTEGRIFOLIA SEED OIL, PROPYLPARABEN, ROSA CANINA FRUIT OIL, SQUALANE, SIMMONDSIA CHINENSIS (JOJOBA) SEED OIL, DISODIUM EDTA, ADENOSINE, BUTYLENE GLYCOL, CERAMIDE NP, FAGUS SYLVATICA BUD EXTRACT, HYDROLYZED COLLAGEN, CHAMOMILLA RECUTITA (MATRICARIA) FLOWER EXTRACT, HIZIKIA FUSIFORME EXTRACT, LAMINARIA JAPONICA EXTRACT, ROSMARINUS OFFICINALIS (ROSEMARY) LEAF EXTRACT, CAPRYLYL GLYCOL, BENZYL ALCOHOL, 1,2-HEXANEDIOL, CAPRYLHYDROXAMIC ACID, SODIUM HYALURONATE, PHENOXYETHANOL, BENZOIC ACID, TROPOLONE, BUTYLPHENYL METHYLPROPIONAL, BENZYL SALICYLATE, HYDROXYCITRONELLAL, ALPHA-ISOMETHYL IONONE, HEXYL CINNAMAL, LINALOOL, CITRONELLOL, LIMONENE